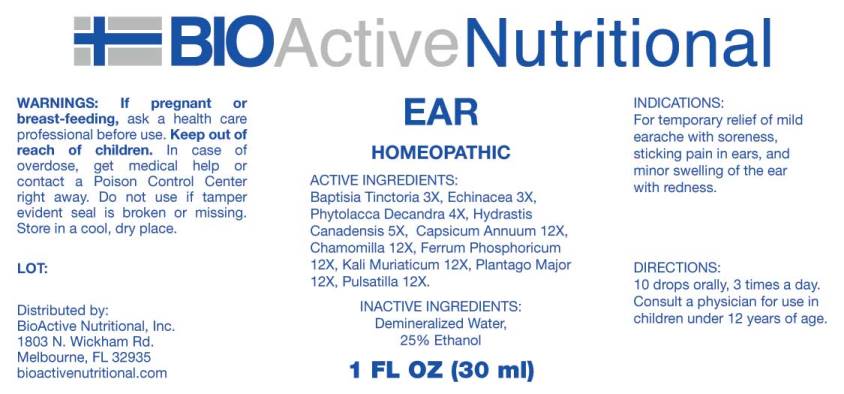 DRUG LABEL: Ear
NDC: 43857-0539 | Form: LIQUID
Manufacturer: BioActive Nutritional, Inc.
Category: homeopathic | Type: HUMAN OTC DRUG LABEL
Date: 20240105

ACTIVE INGREDIENTS: BAPTISIA TINCTORIA ROOT 3 [hp_X]/1 mL; ECHINACEA ANGUSTIFOLIA WHOLE 3 [hp_X]/1 mL; PHYTOLACCA AMERICANA ROOT 4 [hp_X]/1 mL; GOLDENSEAL 5 [hp_X]/1 mL; CAPSICUM 12 [hp_X]/1 mL; MATRICARIA CHAMOMILLA WHOLE 12 [hp_X]/1 mL; FERROSOFERRIC PHOSPHATE 12 [hp_X]/1 mL; POTASSIUM CHLORIDE 12 [hp_X]/1 mL; PLANTAGO MAJOR WHOLE 12 [hp_X]/1 mL; PULSATILLA PRATENSIS WHOLE 12 [hp_X]/1 mL
INACTIVE INGREDIENTS: WATER; ALCOHOL

DRUG FACTS:

ACTIVE INGREDIENTS:

Baptisia Tinctoria 3X, Echinacea (Angustifolia) 3X, Phytolacca Decandra 3X, Hydrastis Canadensis 5X, Capsicum Annuum 12X, Chamomilla 12X, Ferrum Phosphoricum 12X, Kali Muriaticum 12X, Plantago Major 12X, Pulsatilla (Pratensis) 12X.

INDICATIONS:

For temporary relief of mild earache with soreness, sticking pain in ears, and minor swelling of the ear with redness.

WARNINGS:

If pregnant or breast-feeding, ask a health care professional before use.
Keep out of reach of children. In case of overdose, get medical help or contact a Poison Control Center right away.
Do not use if tamper evident seal is broken or missing.
Store in cool, dry place.

KEEP OUT OF REACH OF CHILDREN:

In case of overdose, get medical help or contact a Poison Control Center right away.

DIRECTIONS:

10 drops orally, 3 times a day. Consult a physician for use in children under 12 years of age.

INDICATIONS:

For temporary relief of mild earache with soreness, sticking pain in ears, and minor swelling of the ear with redness.

INACTIVE INGREDIENTS:

Demineralized Water, 25% Ethanol

QUESTIONS:

Distributed by:
BioActive Nutritional, Inc.
1803 N. Wickham Rd.
Melbourne, FL 32935
bioactivenutritional.com

PACKAGE LABEL DISPLAY:

BIOActive Nutritional
EAR
HOMEOPATHIC
1 FL OZ (30 ml)